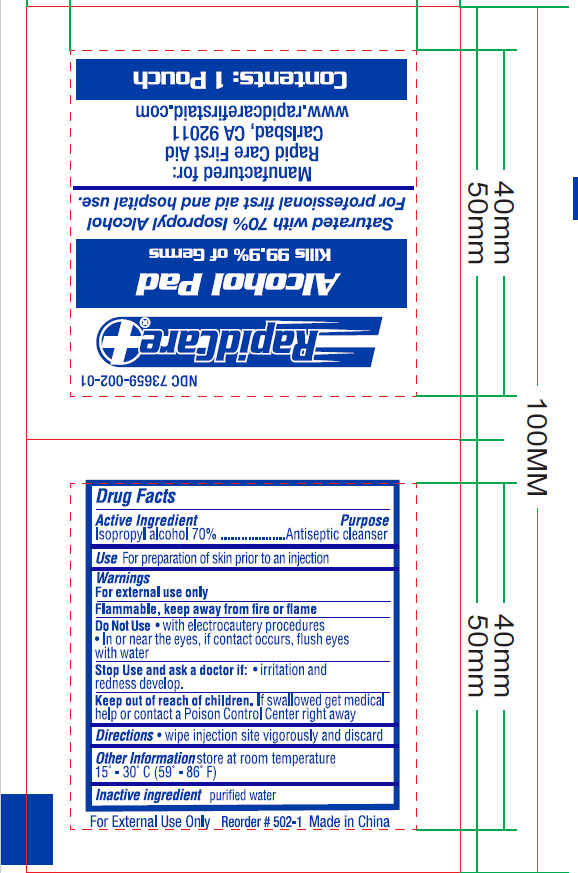 DRUG LABEL: Alcohol Pad
NDC: 72766-007 | Form: SWAB
Manufacturer: Yangzhou Suxiang Medical Instrument Co., Ltd.
Category: otc | Type: HUMAN OTC DRUG LABEL
Date: 20210331

ACTIVE INGREDIENTS: ISOPROPYL ALCOHOL 70 mL/1 1
INACTIVE INGREDIENTS: WATER

ACTIVE INGREDIENT

lsopropyl alcohol 70%

PURPOSE

Antiseptic cleanser

Use

For preparation of skin prior to an injection

WARNINGS

For external use only
Flammable, keep away from fire or flame

DO NOT USE

with electrocautery procedures

ln or near the eyes, if contact occurs, flush eyes with water

Stop Use and ask a doctor if: irritation and redness develop.

Keep out of reach of children. lf swallowed get medical help or contact a Poison Control Center right away.

Directions

wipe injection site vigorously and discard

Other Information

store at room temperature 15°-30°C(59°-86°F)

INACTIVE INGREDIENT

purified water